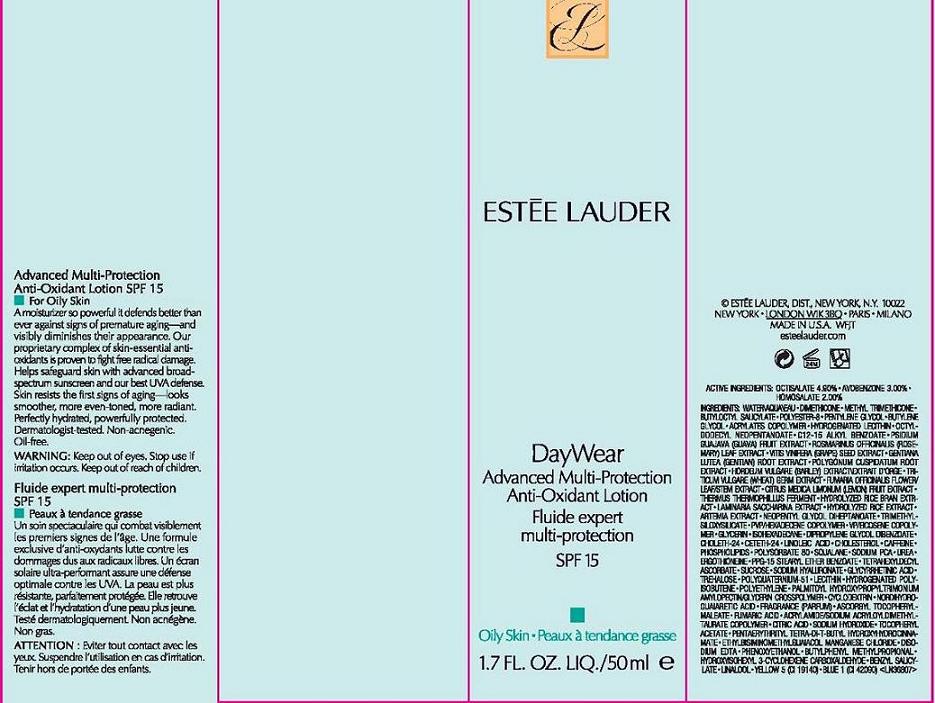 DRUG LABEL: DAYWEAR
NDC: 11559-010 | Form: LOTION
Manufacturer: ESTEE LAUDER INC
Category: otc | Type: HUMAN OTC DRUG LABEL
Date: 20110119

ACTIVE INGREDIENTS: OCTISALATE 4.9 mL/100 mL; AVOBENZONE 3.0 mL/100 mL; HOMOSALATE 2.0 mL/100 mL
INACTIVE INGREDIENTS: WATER; BUTYLENE GLYCOL; DIMETHICONE; GLYCERIN; CHOLESTEROL; SQUALANE; CITRIC ACID MONOHYDRATE; LECITHIN, SOYBEAN; BUTYLATED HYDROXYTOLUENE; PHENOXYETHANOL; POTASSIUM SORBATE

ACTIVE INGREDIENT

ACTIVE INGREDIENTS: OCTISALATE 4.90% [] AVOBENZONE 3.00% [] HOMOSALATE 2.00%

INACTIVE INGREDIENT

INACTIVE INGREDIENTS: INGREDIENTS: WATER\AQUA\EAU [] DIMETHICONE [] METHYL TRIMETHICONE [] BUTYLOCTYL SALICYLATE [] POLYESTER-8 [] PENTYLENE GLYCOL [] BUTYLENE GLYCOL [] ACRYLATES COPOLYMER [] HYDROGENATED LECITHIN [] OCTYLDODECYL NEOPENTANOATE [] C12-15 ALKYL BENZOATE [] PSIDIUM GUAJAVA (GUAVA) FRUIT EXTRACT [] ROSMARINUS OFFICINALIS (ROSEMARY) LEAF EXTRACT [] VITIS VINIFERA (GRAPE) SEED EXTRACT [] GENTIANA LUTEA (GENTIAN) ROOT EXTRACT [] POLYGONUM CUSPIDATUM ROOT EXTRACT [] HORDEUM VULGARE (BARLEY) EXTRACT\EXTRAIT D'ORGE [] TRITICUM VULGARE (WHEAT) GERM EXTRACT [] FUMARIA OFFICINALIS FLOWER/LEAF/STEM EXTRACT [] CITRUS MEDICA LIMONUM (LEMON) FRUIT EXTRACT [] THERMUS THERMOPHILLUS FERMENT [] HYDROLYZED RICE BRAN EXTRACT [] LAMINARIA SACCHARINA EXTRACT [] HYDROLYZED RICE EXTRACT [] ARTEMIA EXTRACT [] NEOPENTYL GLYCOL DIHEPTANOATE [] TRIMETHYLSILOXYSILICATE [] PVP/HEXADECENE COPOLYMER [] VP/EICOSENE COPOLYMER [] GLYCERIN [] ISOHEXADECANE [] DIPROPYLENE GLYCOL DIBENZOATE [] CHOLETH-24 [] CETETH-24 [] LINOLEIC ACID [] CHOLESTEROL [] CAFFEINE [] PHOSPHOLIPIDS [] POLYSORBATE 80 [] SQUALANE [] SODIUM PCA [] UREA [] ERGOTHIONEINE [] PPG-15 STEARYL ETHER BENZOATE [] TETRAHEXYLDECYL ASCORBATE [] SUCROSE [] SODIUM HYALURONATE [] GLYCYRRHETINIC ACID [] TREHALOSE [] POLYQUATERNIUM-51 [] LECITHIN [] HYDROGENATED POLYISOBUTENE [] POLYETHYLENE [] PALMITOYL HYDROXYPROPYLTRIMONIUM AMYLOPECTIN/GLYCERIN CROSSPOLYMER [] CYCLODEXTRIN [] NORDIHYDROGUAIARETIC ACID [] FRAGRANCE (PARFUM) [] ASCORBYL TOCOPHERYL MALEATE [] FUMARIC ACID [] ACRYLAMIDE/SODIUM ACRYLOYLDIMETHYLTAURATE COPOLYMER [] CITRIC ACID [] SODIUM HYDROXIDE [] TOCOPHERYL ACETATE [] PENTAERYTHRITYL TETRA-DI-T-BUTYL HYDROXYHYDROCINNAMATE [] ETHYLBISIMINOMETHYLGUAIACOL MANGANESE CHLORIDE [] DISODIUM EDTA [] BHT [] PHENOXYETHANOL [] BUTYLPHENYL METHYLPROPIONAL [] HYDROXYISOHEXYL 3-CYCLOHEXENE CARBOXALDEHYDE [] BENZYL SALICYLATE [] LINALOOL [] YELLOW 5 (CI 19140) [] BLUE 1 (CI 42090)

WARNINGS

WARNING: KEEP OUT OF EYES. DISCONTINUE USE IF IRRITATION OCCURS.

KEEP OUT OF REACH OF CHILDREN.

PACKAGE LABEL

PRINCIPAL DISPLAY PANEL:

ESTEE LAUDER

DAYWEAR

ADVANCED MULTI-PROTECTION

ANTI-OXIDANT LOTION

SPF 15

FOR OILY SKIN

1.7 FL LIQ OZ/ 50 ML

ESTEE LAUDER DISTR

NY NY 10022